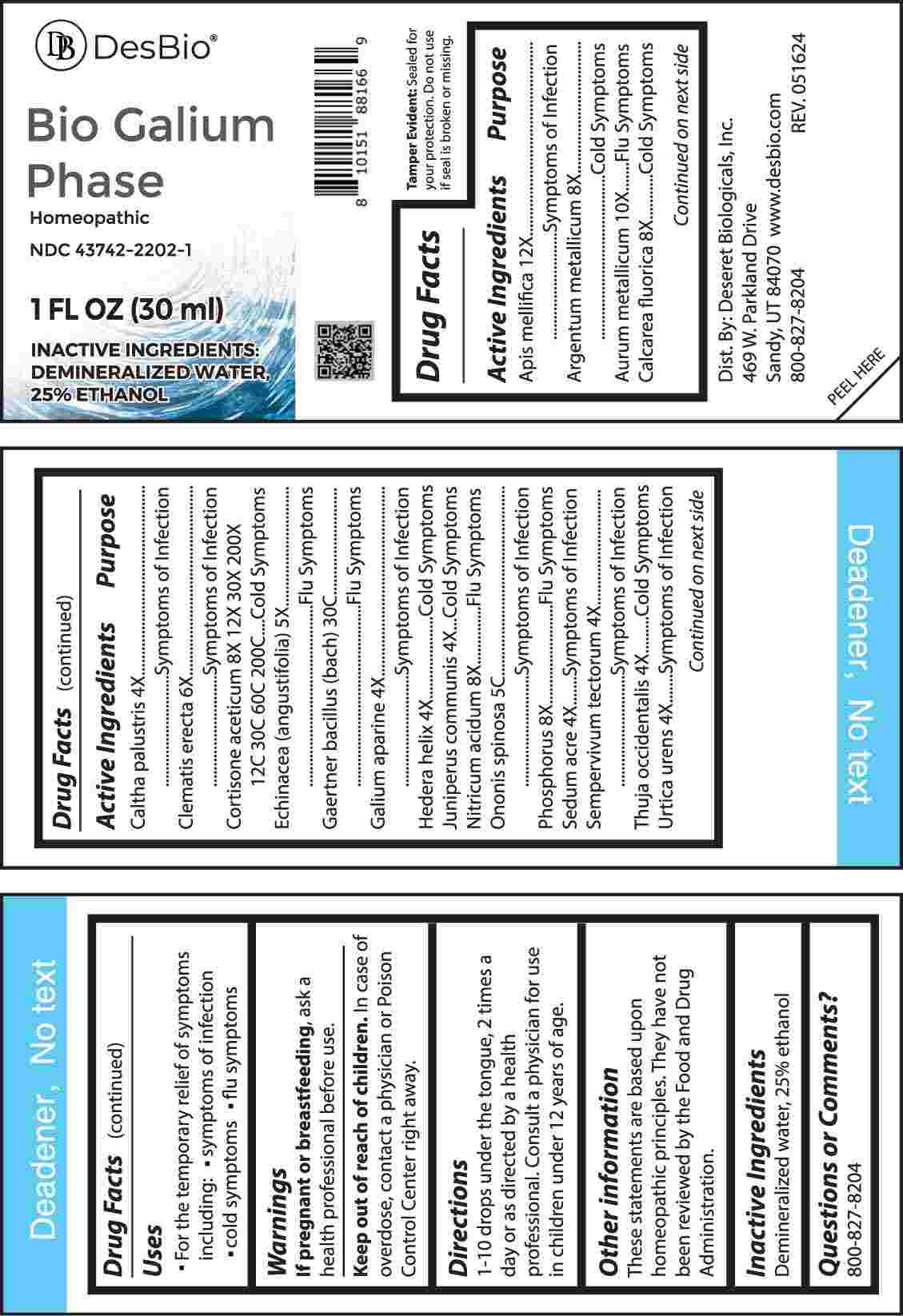 DRUG LABEL: Bio Galium Phase
NDC: 43742-2202 | Form: LIQUID
Manufacturer: Deseret Biologicals, Inc.
Category: homeopathic | Type: HUMAN OTC DRUG LABEL
Date: 20240815

ACTIVE INGREDIENTS: APIS MELLIFERA 12 [hp_X]/1 mL; SILVER 8 [hp_X]/1 mL; GOLD 10 [hp_X]/1 mL; CALCIUM FLUORIDE 8 [hp_X]/1 mL; CALTHA PALUSTRIS WHOLE 4 [hp_X]/1 mL; CLEMATIS RECTA FLOWERING TOP 6 [hp_X]/1 mL; CORTISONE ACETATE 8 [hp_X]/1 mL; ECHINACEA ANGUSTIFOLIA WHOLE 5 [hp_X]/1 mL; SALMONELLA ENTERICA ENTERICA SEROVAR ENTERITIDIS 30 [hp_C]/1 mL; GALIUM APARINE WHOLE 4 [hp_X]/1 mL; HEDERA HELIX FLOWERING TWIG 4 [hp_X]/1 mL; JUNIPER BERRY 4 [hp_X]/1 mL; NITRIC ACID 8 [hp_X]/1 mL; ONONIS SPINOSA WHOLE 5 [hp_C]/1 mL; PHOSPHORUS 8 [hp_X]/1 mL; SEDUM ACRE WHOLE 4 [hp_X]/1 mL; SEMPERVIVUM TECTORUM LEAF 4 [hp_X]/1 mL; THUJA OCCIDENTALIS LEAFY TWIG 4 [hp_X]/1 mL; URTICA URENS WHOLE 4 [hp_X]/1 mL
INACTIVE INGREDIENTS: WATER; ALCOHOL

DRUG FACTS:

ACTIVE INGREDIENTS:

Apis Mellifica 12X, Argentum Metallicum 8X, Aurum Metallicum 10X, Calcarea Fluorica 8X, Caltha Palustris 4X, Clematis Erecta 6X, Cortisone Aceticum 8X, 12X, 30X, 200X, 12C, 30C, 60C, 200C, Echinacea (Angustifolia) 5X, Gaertner Bacillus (Bach) 30C, Galium Aparine 4X, Hedera Helix 4X, Juniperus Communis 4X, Nitricum Acidum 8X, Ononis Spinosa 5C, Phosphorus 8X, Sedum Acre 4X, Sempervivum Tectorum 4X, Thuja Occidentalis 4X, Urtica Urens 4X.

PURPOSE:

Apis Mellifica – Symptoms of Infection, Argentum Metallicum – Cold Symptoms, Aurum Metallicum – Flu Symptoms, Calcarea Fluorica – Cold Symptoms, Caltha Palustris – Symptoms of Infection, Clematis Erecta – Symptoms of Infection, Cortisone Aceticum – Cold Symptoms, Echinacea (Angustifolia) – Flu Symptoms, Gaertner Bacillus (Bach) – Flu Symptoms, Galium Aparine – symptoms of Infection, Hedera Helix – Cold Symptoms, Juniperus Communis – Cold Symptoms, Nitricum Acidum – Flu Symptoms, Ononis Spinosa – Symptoms of Infection, Phosphorus – Flu Symptoms, Sedum Acre – Symptoms of Infection, Sempervivum Tectorum – Symptoms of Infection, Thuja Occidentalis – Cold Symptoms, Urtica Urens – Symptoms of Infection

USES:

• For the temporary relief of symptoms including:

• symptoms of infection • cold symptoms • flu symptoms

These statements are based upon homeopathic principles. They have not been reviewed by the Food and Drug Administration.

WARNINGS:

If pregnant or breast-feeding, ask a health professional before use.

Keep out of reach of children. In case of overdose, contact a physician or Poison Control Center right away.

Tamper Evident: Sealed for your protection. Do not use if seal is broken or missing.

KEEP OUT OF REACH OF CHILDREN:

In case of overdose, contact a physician or Poison Control Center right away.

DIRECTONS:

1-10 drops under the tongue, 2 times a day or as directed by a health professional. Consult a physician for use in children under 12 years of age.

INACTIVE INGREDIENTS:

Demineralized water, 25% ethanol

QUESTIONS:

Dist. By: Deseret Biologicals, Inc.

469 W. Parkland Drive

Sandy, UT 84070

www.desbio.com

800-827-8204

PACKAGE LABEL DISPLAY:

DesBio

Bio Galium Phase

Homeopathic

NDC 43742-2202-1

1 FL OZ (30 ml)